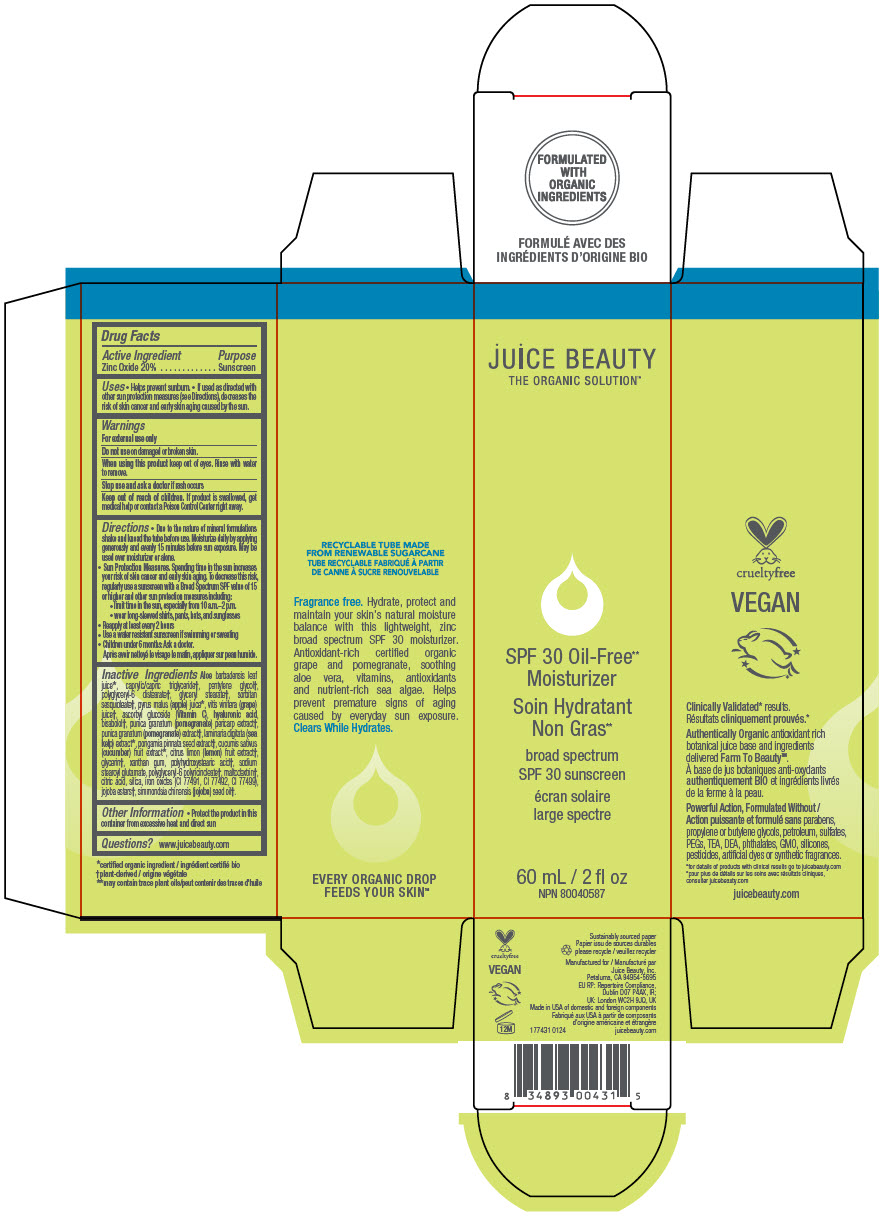 DRUG LABEL: SPF 30 Oil-Free Moisturizer
NDC: 55165-0202 | Form: LOTION
Manufacturer: Juice Beauty
Category: otc | Type: HUMAN OTC DRUG LABEL
Date: 20241217

ACTIVE INGREDIENTS: Zinc Oxide 20 g/100 mL
INACTIVE INGREDIENTS: ALOE VERA LEAF; MEDIUM-CHAIN TRIGLYCERIDES; pentylene glycol; polyglyceryl-6 distearate; GLYCERYL 1-STEARATE; sorbitan sesquioleate; WINE GRAPE JUICE; apple juice; ASCORBYL GLUCOSIDE; hyaluronic acid; LEVOMENOL; POMEGRANATE FRUIT RIND; POMEGRANATE; LAMINARIA DIGITATA; PONGAMIA PINNATA SEED; CUCUMBER; LEMON; glycerin; xanthan gum; POLYHYDROXYSTEARIC ACID (2300 MW); sodium stearoyl glutamate; polyglyceryl-6 polyricinoleate; maltodextrin; CITRIC ACID MONOHYDRATE; SILICON DIOXIDE; FERRIC OXIDE RED; FERRIC OXIDE YELLOW; FERROSOFERRIC OXIDE; JOJOBA OIL, RANDOMIZED; JOJOBA OIL

SPF 30 Oil-Free Moisturizer

Drug Facts

Active Ingredient

Zinc Oxide 20%

Purpose

Sunscreen

Uses

- Helps prevent sunburn.
- If used as directed with other sun protection measures (see Directions), decreases the risk of skin cancer and early skin aging caused by the sun.

Warnings

For external use only

Do not use on damaged or broken skin.

When using this product keep out of eyes. Rinse with water to remove.

Stop use and ask a doctor if rash occurs

Keep out of reach of children. If product is swallowed, get medical help or contact a Poison Control Center right away.

Directions

- Due to the nature of mineral formulations shake and knead the tube before use. Moisturize daily by applying generously and evenly 15 minutes before sun exposure. May be used over moisturizer or alone.
- Sun Protection Measures. Spending time in the sun increases your risk of skin cancer and early skin aging. To decrease this risk, regularly use a sunscreen with a Broad Spectrum SPF value of 15 or higher and other sun protection measures including:
  - limit time in the sun, especially from 10 a.m.–2 p.m.
  - wear long-sleeved shirts, pants, hats, and sunglasses
- Reapply at least every 2 hours
- Use a water resistant sunscreen if swimming or sweating
- Children under 6 months: Ask a doctor.
  Après avoir nettoyé le visage le matin, appliquer sur peau humide.

Inactive Ingredients

Aloe barbadensis leaf juice [certified organic ingredient] , caprylic/capric triglyceride [plant-derived] , pentylene glycol, polyglyceryl-6 distearate, glyceryl stearate, sorbitan sesquioleate, pyrus malus (apple) juice, vitis vinifera (grape) juice, ascorbyl glucoside (Vitamin C), hyaluronic acid, bisabolol, punica granatum (pomegranate) pericarp extract, punica granatum (pomegranate) extract, laminaria digitata (sea kelp) extract, pongamia pinnata seed extract, cucumis sativus (cucumber) fruit extract, citrus limon (lemon) fruit extract, glycerin, xanthan gum, polyhydroxystearic acid, sodium stearoyl glutamate, polyglyceryl-6 polyricinoleate, maltodextrin, citric acid, silica, iron oxides (CI 77491, CI 77492, CI 77499), jojoba esters, simmondsia chinensis (jojoba) seed oil.

Other Information

- Protect the product in this container from excessive heat and direct sun

Questions?

www.juicebeauty.com

PRINCIPAL DISPLAY PANEL - 60 mL Tube Carton

jUiCE BEAUTY
THE ORGANIC SOLUTION™

SPF 30 Oil-Free**
Moisturizer

broad spectrum
SPF 30 sunscreen

60 mL / 2 fl oz
NPN 80040587